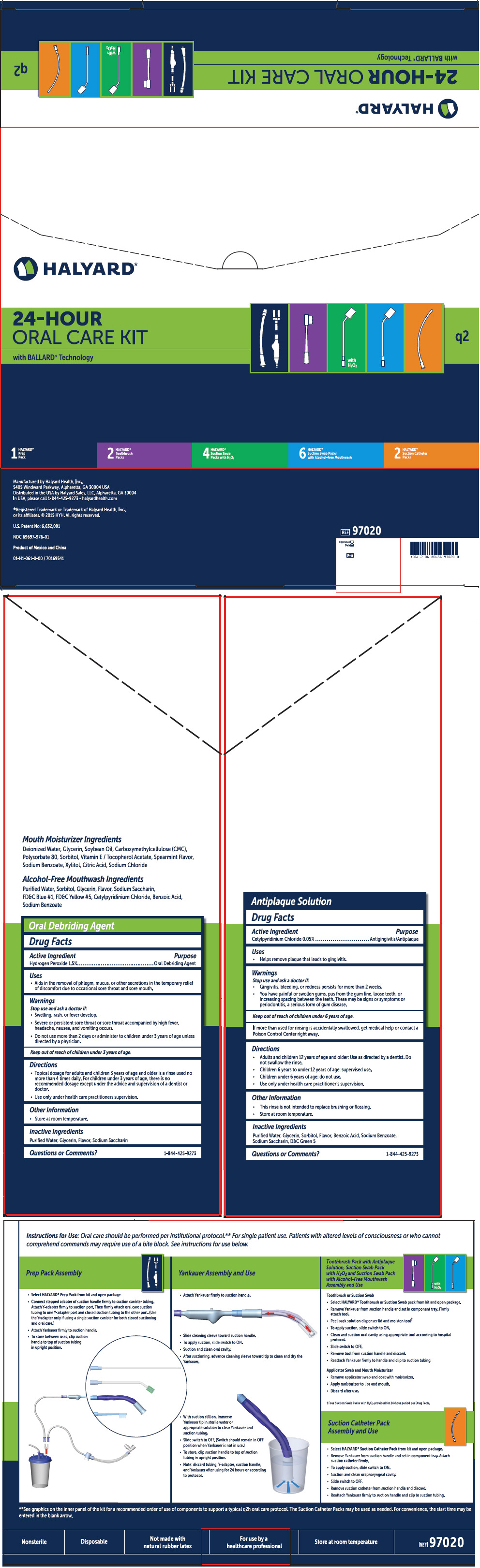 DRUG LABEL: Q2 Oral Care Kit 
NDC: 69697-983 | Form: KIT | Route: ORAL
Manufacturer: Halyard Health
Category: otc | Type: HUMAN OTC DRUG LABEL
Date: 20160125

ACTIVE INGREDIENTS: Hydrogen peroxide 0.015 mg/1 mL
INACTIVE INGREDIENTS: Water; Glycerin; Mint; Saccharin Sodium Dihydrate

Halyard
24-Hour Oral Care Kit

Drug Facts

Active Ingredient

Hydrogen Peroxide 1.5%

Purpose

Oral Debriding Agent

Uses

- Aids in the removal of phlegm, mucus, or other secretions in the temporary relief of discomfort due to occasional sore throat and sore mouth.

Warnings

Stop use and ask a doctor if

- Swelling, rash, or fever develop.
- Severe or persistent sore throat or sore throat accompanied by high fever, headache, nausea, and vomiting occurs.

- Do not use more than 2 days or administer to children under 3 years of age unless directed by a physician.

Keep out of reach of children under 3 years of age.

Directions

- Topical dosage for adults and children 3 years of age and older is a rinse used no more than 4 times daily. For children under 3 years of age, there is no recommended dosage except under the advice and supervision of a dentist or doctor.
- Use only under health care practitioners supervision.

Other Information

- Store at room temperature.

Inactive Ingredients

Purified Water, Glycerin, Flavor, Sodium Saccharin

Questions or Comments?

1-844-425-9273

Distributed in the U.S. by Kimberly-Clark Global Sales, LLC, Roswell, GA 30076 USA

PRINCIPAL DISPLAY PANEL - Kit Carton

HALYARD*

24-HOUR
ORAL CARE KIT

with BALLARD* Technology

with
H2O2

q2

1
HALYARD*
Prep
Pack

2
HALYARD*
Toothbrush
Packs

4
HALYARD*
Suction Swab
Packs with H2O2

6
HALYARD*
Suction Swab Packs
with Alcohol-Free Mouthwash

2
HALYARD*
Suction Catheter
Packs